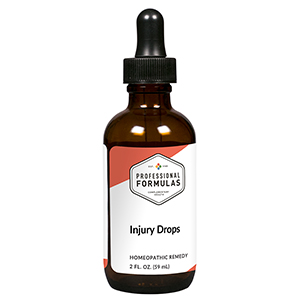 DRUG LABEL: Injury Drops
NDC: 63083-2034 | Form: LIQUID
Manufacturer: Professional Complementary Health Formulas
Category: homeopathic | Type: HUMAN OTC DRUG LABEL
Date: 20190815

ACTIVE INGREDIENTS: ECHINACEA PURPUREA WHOLE 3 [hp_X]/59 mL; ARNICA MONTANA WHOLE 3 [hp_X]/59 mL; CALENDULA OFFICINALIS FLOWERING TOP 3 [hp_X]/59 mL; BELLIS PERENNIS WHOLE 6 [hp_X]/59 mL; BERBERIS VULGARIS ROOT BARK 6 [hp_X]/59 mL; BOS TAURUS BONE MARROW 6 [hp_X]/59 mL; RHODODENDRON TOMENTOSUM LEAFY TWIG 6 [hp_X]/59 mL; PHOSPHORUS 6 [hp_X]/59 mL; SILICON DIOXIDE 6 [hp_X]/59 mL; COMFREY ROOT 6 [hp_X]/59 mL; HYPERICUM PERFORATUM WHOLE 6 [hp_X]/59 mL; RUTA GRAVEOLENS FLOWERING TOP 6 [hp_X]/59 mL; TOXICODENDRON PUBESCENS LEAF 12 [hp_X]/59 mL
INACTIVE INGREDIENTS: ALCOHOL; WATER

C34

ACTIVE INGREDIENTS

Echinacea purpurea 3X
Arnica montana 3X, 6X, 12X, 100X, 1000X
Calendula officinalis 3X, 12X, 30X, 100X, 1000X
Bellis perennis 6X
Berberis vulgaris 6X
Bone marrow 6X
Ledum palustre 6X
Phosphorus 6X
Silicea 6X
Symphytum officinale 6X
Hypericum perforatum 6X, 12X, 30X, 60X
Ruta graveolens 6X, 12X, 30X
Rhus toxicodendron 12X

QUESTIONS

Professional Formulas

PO Box 2034 Lake Oswego, OR 97035

INDICATIONS

For the temporary relief of minor joint or muscle pain, inflammation, minor sprains or strains, bruises, or minor cuts or scrapes.*

PURPOSE

*Claims based on traditional homeopathic practice, not accepted medical evidence. Not FDA evaluated.

WARNINGS

In case of overdose, get medical help or contact a poison control center right away.

Keep out of the reach of children.

PREGNANCY OR BREAST FEEDING

If pregnant or breastfeeding, ask a healthcare professional before use.

DIRECTIONS

Place drops under tongue 30 minutes before/after meals. Adults and children 12 years and over: Take 10 drops up to 3 times per day for up to 6 weeks. For immediate onset of symptoms, take 10 to 15 drops every 15 minutes up to 3 hours. For less severe symptoms, take 10-15 drops hourly up to 8 hours. Consult a physician for use in children under 12 years of age.

OTHER INFORMATION

Tamper resistant. If seal is broken, do not use. After opening, close container tightly and store at room temperature away from heat.

INACTIVE INGREDIENTS

20% ethanol, purified water.

LABEL

Est 1985

Professional Formulas

Complementary Health

Injury Drops

Homeopathic Remedy

2 FL. OZ. (59 mL)